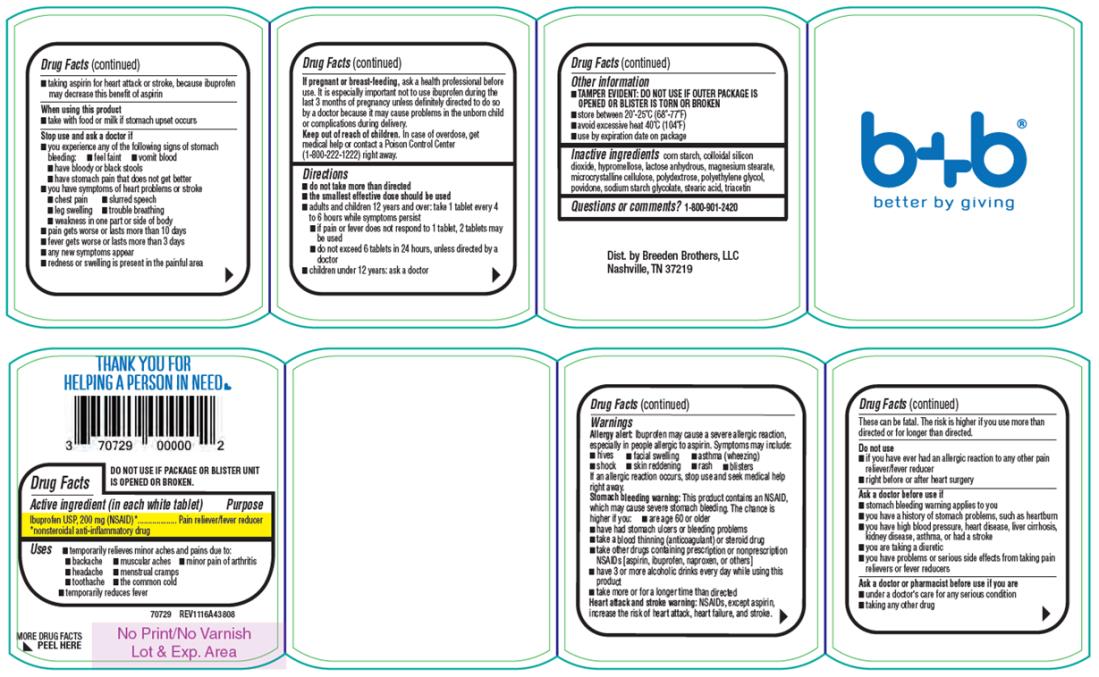 DRUG LABEL: Dye Free Ibuprofen
NDC: 70729-002 | Form: TABLET
Manufacturer: Breeden Brothers, LLC
Category: otc | Type: HUMAN OTC DRUG LABEL
Date: 20170215

ACTIVE INGREDIENTS: IBUPROFEN 200 mg/1 1
INACTIVE INGREDIENTS: HYPROMELLOSE, UNSPECIFIED; TRIACETIN; MAGNESIUM STEARATE; STEARIC ACID; STARCH, CORN; MICROCRYSTALLINE CELLULOSE; POLYDEXTROSE; POLYETHYLENE GLYCOL, UNSPECIFIED; POVIDONE, UNSPECIFIED; ANHYDROUS LACTOSE; SILICON DIOXIDE

Dye Free Ibuprofen

Drug Facts

Active ingredient (in each white tablet)

Ibuprofen USP, 200 mg (NSAID)*

Purpose

Pain reliever/fever reducer *nonsteroidal anti-inflammatory drug

Uses

_ temporarily relieves minor aches and pains due to:

_ backache _ muscular aches _ minor pain of arthritis

_ headache _ menstrual cramps

_ toothache _ the common cold

_ temporarily reduces fever

Drug Facts (continued)

Warnings

Allergy alert: Ibuprofen may cause a severe allergic reaction, especially in people allergic to aspirin. Symptoms may include:

_ hives _ facial swelling _ asthma (wheezing)

_ shock _ skin reddening _ rash _ blisters

If an allergic reaction occurs, stop use and seek medical help right away.

Stomach bleeding warning: This product contains an NSAID, which may cause severe stomach bleeding. The chance is higher if you:

_ are age 60 or older

_ have had stomach ulcers or bleeding problems

_ take a blood thinning (anticoagulant) or steroid drug

_ take other drugs containing prescription or nonprescription NSAIDs [aspirin, ibuprofen, naproxen, or others]

_ have 3 or more alcoholic drinks every day while using this product

_ take more or for a longer time than directed

Heart attack and stroke warning: NSAIDs, except aspirin, increase the risk of heart attack, heart failure, and stroke.

Drug Facts (continued)

These can be fatal. The risk is higher if you use more than directed or for longer than directed.

Do not use

_ if you have ever had an allergic reaction to any other pain reliever/fever reducer

_ right before or after heart surgery

Ask a doctor before use if

_ stomach bleeding warning applies to you

_ you have a history of stomach problems, such as heartburn

_ you have high blood pressure, heart disease, liver cirrhosis, kidney disease, asthma, or had a stroke

_ you are taking a diuretic

_ you have problems or serious side effects from taking pain relievers or fever reducers

Ask a doctor or pharmacist before use if you are

_ under a doctor's care for any serious condition

_ taking any other drug

Drug Facts (continued)

_ taking aspirin for heart attack or stroke, because ibuprofen may decrease this benefit of aspirin

When using this product

_ take with food or milk if stomach upset occurs

Stop use and ask a doctor if

_ you experience any of the following signs of stomach bleeding:

_ feel faint _ vomit blood

_ have bloody or black stools

_ have stomach pain that does not get better

_ you have symptoms of heart problems or stroke

_ chest pain _ slurred speech

_ leg swelling _ trouble breathing

_ weakness in one part or side of body

_ pain gets worse or lasts more than 10 days

_ fever gets worse or lasts more than 3 days

_ any new symptoms appear

_ redness or swelling is present in the painful area

Drug Facts (continued)

If pregnant or breast-feeding,

ask a health professional before use. It is especially important not to use ibuprofen during the last 3 months of pregnancy unless definitely directed to do so by a doctor because it may cause problems in the unborn child or complications during delivery.

Keep out of reach of children.

In case of overdose, get medical help or contact a Poison Control Center (1-800-222-1222) right away.

Directions

_ do not take more than directed

_ the smallest effective dose should be used

_ adults and children 12 years and over: take 1 tablet every 4 to 6 hours while symptoms persist

_ if pain or fever does not respond to 1 tablet, 2 tablets may be used

_ do not exceed 6 tablets in 24 hours, unless directed by a doctor

_ children under 12 years: ask a doctor

Drug Facts (continued)

Other information

_ TAMPER EVIDENT: DO NOT USE IF OUTER PACKAGE IS OPENED OR BLISTER IS TORN OR BROKEN

_ store between 20°-25°C (68°-77°F)

_ avoid excessive heat 40°C (104°F)

_ use by expiration date on package

Inactive ingredients

corn starch, colloidal silicon dioxide, hypromellose, lactose anhydrous, magnesium stearate, microcrystalline cellulose, polydextrose, polyethylene glycol, povidone, sodium starch glycolate, stearic acid, triacetin

Questions or comments?

1-800-901-2420

Dist. by Breeden Brothers, LLC

Nashville, TN 37219

PRINCIPAL DISPLAY PANEL

b+b
better by giving